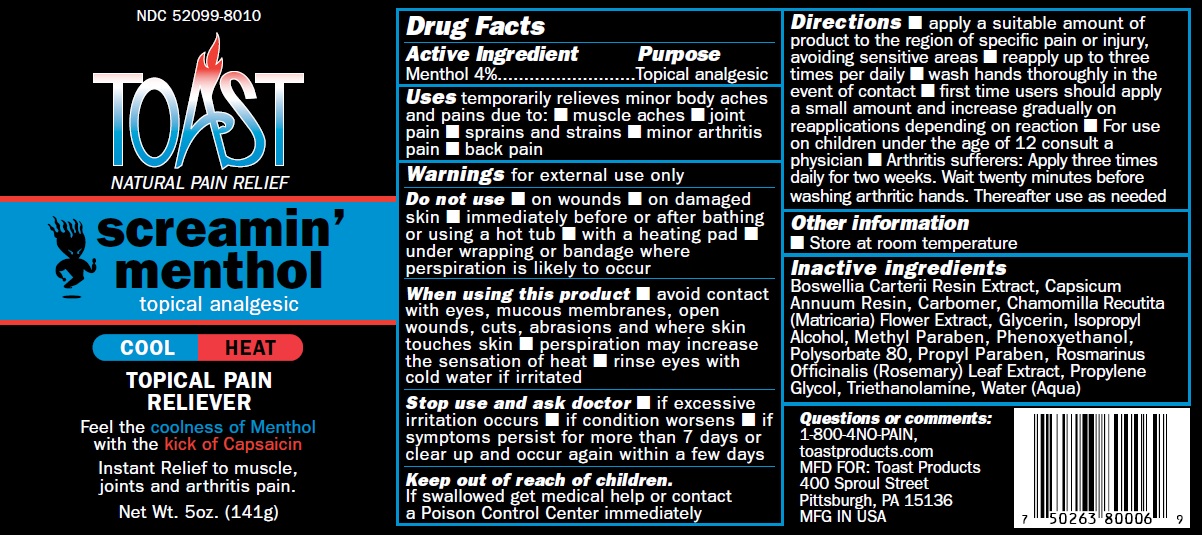 DRUG LABEL: SCREAMIN MENTHOL TOAST
                
NDC: 52099-8010 | Form: CREAM
Manufacturer: Q.A. Laboratories
Category: otc | Type: HUMAN OTC DRUG LABEL
Date: 20220117

ACTIVE INGREDIENTS: MENTHOL, UNSPECIFIED FORM 4 g/100 g
INACTIVE INGREDIENTS: GLYCERIN; CHAMOMILE; ISOPROPYL ALCOHOL; POLYSORBATE 80; METHYLPARABEN; FRANKINCENSE; CAPSICUM OLEORESIN; PROPYLENE GLYCOL; CARBOMER HOMOPOLYMER TYPE B (ALLYL SUCROSE CROSSLINKED); ROSEMARY OIL; WATER; TROLAMINE

Drug Facts

Active Ingredient Purpose
Menthol 4%..........................Topical analgesic

PURPOSE

Uses temporarily relieves minor body aches and pains due to: ar thritis pain, back pain, muscle aches,joint pain.

Warnings for external use only

Do not use immediately before or after bathing or using a hot tub, in conjunction with heating pad,under wrapping or bandage where perspiration is likely to occur.

Stop use and ask doctor if excessive irritation occurs, if condition worsens, if symptoms persist for more than 7 days or clear up and occur again within a few days.

When using this product avoid contact with eyes, mucous membranes, open wounds, cuts, abrasions and where skin touches skin, perspiration may increase the sensation of heat, rinse eyes with cold water if irritated.

Stop use and ask doctor if excessive irritation occurs, if condition worsens ,if symptoms persist for more than 7 days or clear up and occur again within a few days.

Keep out of reach of children. If swallowed get medical help or contact a Poison Control Center immediately

INDICATIONS AND USAGE

Directions apply a suitable amount of product to the region of specific pain or injury, avoiding sensitive areas reapply up to three times per daily, wash hands thoroughly in the event of contact. First time users should apply a small amount and increase gradually on reapplications depending on reaction. For use on children under the age of 12 consult a physician Arthritis suf ferers: Apply three times daily for two weeks. Wait twenty minutes before washing arthritic hands. Thereafter use as needed.

Other information
Store at room temperature

Inactive ingredients
Boswellia Carterii Resin Extract, Capsicum Annuum Resin, Carbomer, Chamomilla Recutita (Matricaria) Flower Extract, Glycerin, Isopropyl Alcohol, Polysorbate 80, Rosmarinus Officinalis (Rosemary) Leaf Oil, Propylene Glycol, Triethanolamine, Water (Aqua)

Questions or comments:
1-800-4NO-PAIN,
toastproducts.com
MFD FOR: Toast Products
400 Sproul Street,
Pittsburgh, PA 15136
MFG IN USA

DOSAGE AND ADMINISTRATION

apply to the region of specific pain or injury